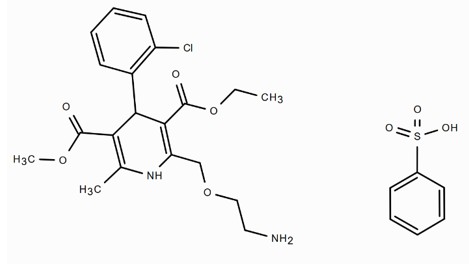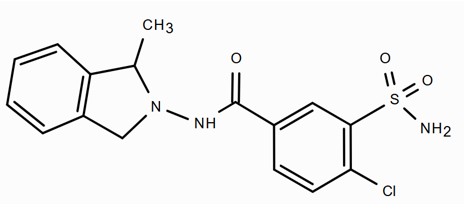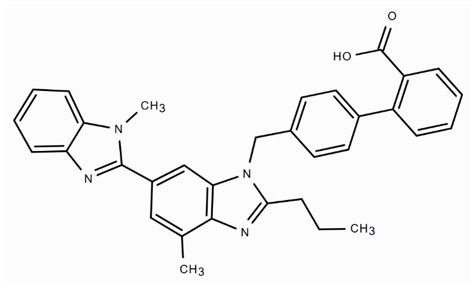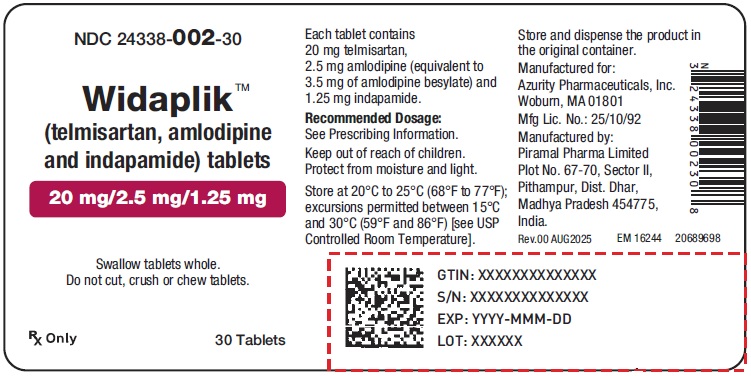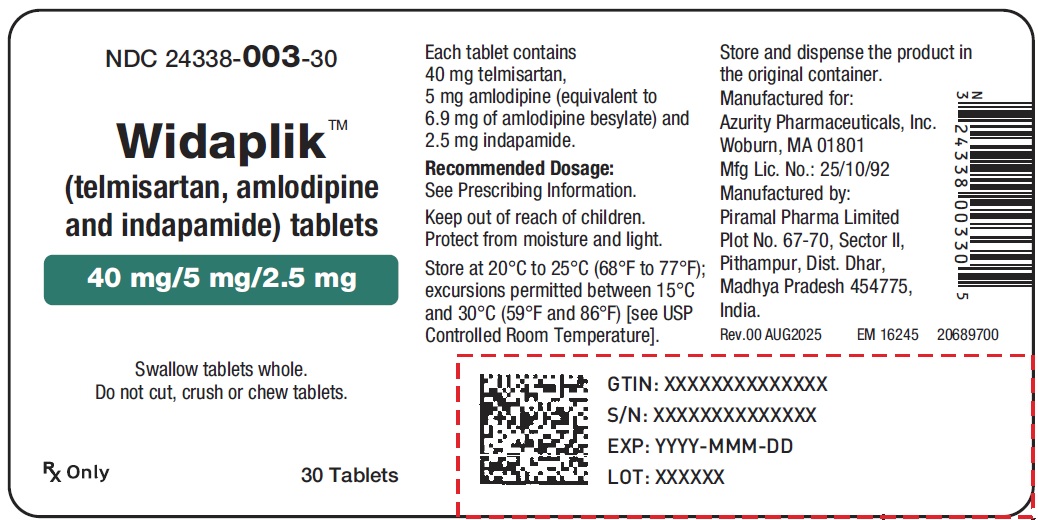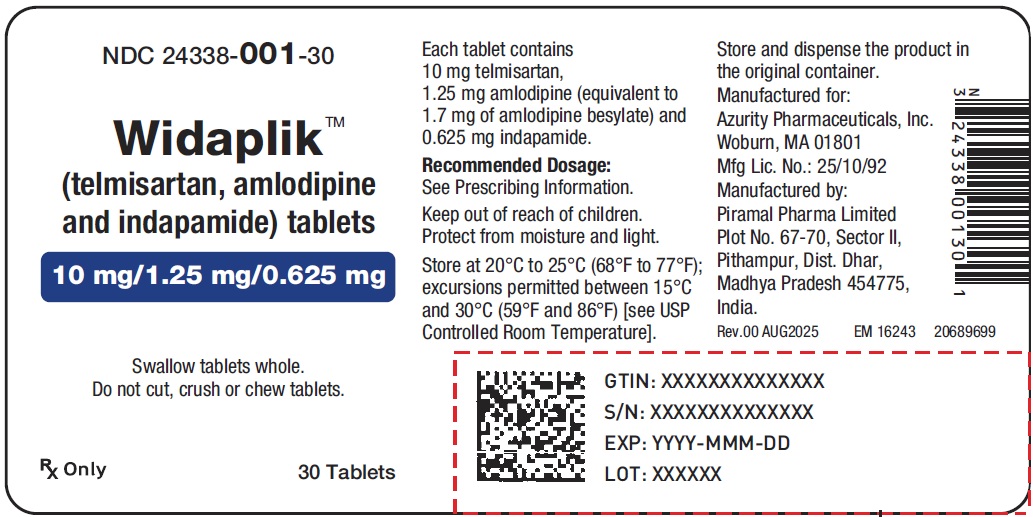 DRUG LABEL: WIDAPLIK
NDC: 24338-001 | Form: TABLET
Manufacturer: Azurity Pharmaceuticals, Inc.
Category: prescription | Type: Human Prescription Drug Label
Date: 20250820

ACTIVE INGREDIENTS: TELMISARTAN 10 mg/1 1; AMLODIPINE BESYLATE 1.25 mg/1 1; INDAPAMIDE 0.625 mg/1 1
INACTIVE INGREDIENTS: MICROCRYSTALLINE CELLULOSE 101; MANNITOL; SODIUM HYDROXIDE; POVIDONE; MEGLUMINE; CROSCARMELLOSE SODIUM; MAGNESIUM STEARATE; STARCH, CORN

HIGHLIGHTS OF PRESCRIBING INFORMATION

These highlights do not include all the information needed to use WIDAPLIK™ safely and effectively. See full prescribing information for WIDAPLIK.
WIDAPLIK (telmisartan, amlodipine and indapamide) tablets, for oral use
Initial U.S. Approval: 2025

WARNING: FETAL TOXICITY

See full prescribing information for complete boxed warning.
• When pregnancy is detected, discontinue WIDAPLIK as soon as possible (5.1, 8.1)
• Drugs that act directly on the renin-angiotensin-aldosterone system can cause injury and death to the developing fetus (5.1, 8.1)

1 INDICATIONS AND USAGE

WIDAPLIK is a combination tablet of telmisartan, an angiotensin II receptor blocker, amlodipine, a dihydropyridine calcium channel blocker and indapamide, a thiazide-like diuretic. Widaplik is indicated for the treatment of hypertension, including as initial treatment, to lower blood pressure. (1) Lowering blood pressure reduces the risk of fatal and nonfatal cardiovascular events, primarily strokes and myocardial infarctions. (1)

2 DOSAGE AND ADMINISTRATION

For initial treatment of hypertension, start with Widaplik (10 mg/ 1.25 mg/0.625 mg) or Widaplik (20 mg/2.5 mg/1.25 mg) orally once daily. Titrate up to a maximum dose of Widaplik (40 mg/5 mg/2.5 mg) orally once daily. (2.2) Dosage may be increased after 2 weeks to a maximum dose of 40 mg/5 mg/2.5 mg orally once daily to achieve more rapid control. (2.1)
Almost all of the antihypertensive effect is apparent within 2 weeks of initiating treatment. (2.1)

3 DOSAGE FORMS AND STRENGTHS

Tablets: (telmisartan/amlodipine/indapamide) 10 mg/1.25 mg/ 0.625 mg, 20 mg/2.5 mg/1.25 mg, 40 mg/5 mg/2.5 mg (3)

4 CONTRAINDICATIONS

- Known hypersensitivity (e.g., anaphylaxis or angioedema) to telmisartan, amlodipine, indapamide, or to other sulfonamide-derived drugs, or to any other component of this product (4)
- Do not co-administer aliskiren with Widaplik in patients with diabetes (4)
- Anuria (4)

5 WARNINGS AND PRECAUTIONS

- Hypotension: Correct volume depletion prior to initiation (5.2)
- Electrolyte and Glucose Imbalances: Monitor serum electrolytes and glucose (5.3)
- Impaired Renal Function: Monitor renal function (5.4)
- Acute angle closure glaucoma can develop (5.5)
- Hyperuricemia may occur (5.6)

6 ADVERSE REACTIONS

The most common adverse reaction is symptomatic hypotension. Low sodium and potassium values were recorded more often with Widaplik compared to placebo (6.1).
To report SUSPECTED ADVERSE REACTIONS, contact Azurity Pharmaceuticals, Inc. at 1-800-461-7449 or FDA at 1-800-FDA-1088 or www.fda.gov/medwatch.

7 DRUG INTERACTIONS

- NSAIDs: Increased risk of renal impairment and loss of anti-hypertensive effect (7.1)
- If simvastatin is co-administered with Widaplik, do not exceed doses greater than 20 mg daily of simvastatin (7.2)
- Do not co-administer aliskiren with Widaplik in patients with diabetes (7.1)

8 USE IN SPECIFIC POPULATIONS

- Lactation: Breastfeeding is not recommended (8.2)
- Geriatric Patients: Severe cases of hyponatremia, accompanied by hypokalemia have been reported with use of indapamide in elderly females; consider initiation at lower doses for patients ≥65 years of age (8.5)
- Hepatic Impairment: Monitor carefully and start treatment at low doses (8.6)

FULL PRESCRIBING INFORMATION

WARNING: FETAL TOXICITY

When pregnancy is detected, discontinue Widaplik as soon as possible [see Warnings and Precautions (5.1) and Use in Specific Populations (8.1)].

Drugs that act directly on the renin-angiotensin-aldosterone system can cause injury and death to the developing fetus [see Warnings and Precautions (5.1) and Use in Specific Populations (8.1)].

1 INDICATIONS AND USAGE

Widaplik (telmisartan/amlodipine/indapamide) is indicated for the treatment of hypertension in adult patients, to lower blood pressure. Widaplik may be used as initial therapy in patients likely to need multiple drugs to achieve blood pressure goals. Lowering blood pressure reduces the risk of fatal and nonfatal cardiovascular events, primarily strokes and myocardial infarctions. These benefits have been seen in controlled trials of antihypertensive drugs from a wide variety of pharmacologic classes including angiotensin II receptor blockers, dihydropyridine calcium channel blockers and thiazide-like diuretics. There are no controlled trials demonstrating risk reduction with Widaplik.

Control of high blood pressure should be part of comprehensive cardiovascular risk management, including, as appropriate, lipid control, diabetes management, antithrombotic therapy, smoking cessation, exercise, and limited sodium intake. Many patients will require more than one drug to achieve blood pressure goals. For specific advice on goals and management, see published guidelines, such as those of the National High Blood Pressure Education Program’s Joint National Committee on Prevention, Detection, Evaluation, and Treatment of High Blood Pressure (JNC).

Numerous antihypertensive drugs, from a variety of pharmacologic classes and with different mechanisms of action, have been shown in randomized controlled trials to reduce cardiovascular morbidity and mortality, and it can be concluded that it is blood pressure reduction, and not some other pharmacologic property of the drugs, that is largely responsible for those benefits. The largest and most consistent cardiovascular outcome benefit has been a reduction in the risk of stroke, but reductions in myocardial infarction and cardiovascular mortality also have been seen regularly.

Elevated systolic or diastolic pressure causes increased cardiovascular risk, and the absolute risk increase per mmHg is greater at higher blood pressures, so that even modest reductions of severe hypertension can provide substantial benefit. Relative risk reduction from blood pressure reduction is similar across populations with varying absolute risk, so the absolute benefit is greater in patients who are at higher risk independent of their hypertension (for example, patients with diabetes or hyperlipidemia), and such patients would be expected to benefit from more aggressive treatment to a lower blood pressure goal.

Some antihypertensive drugs have smaller blood pressure effects (as monotherapy) in black patients, and many antihypertensive drugs have additional approved indications and effects (e.g., on angina, heart failure, or diabetic kidney disease). These considerations may guide selection of therapy.

Patients with moderate or severe hypertension are at relatively high risk for cardiovascular events (such as strokes, heart attacks, and heart failure), kidney failure, and vision problems, so prompt treatment is clinically relevant. Consider the patient's baseline blood pressure, the target goal, and the incremental likelihood of achieving the goal with a triple combination product compared with mono- or dual therapy when deciding whether to use Widaplik as initial therapy. Individual blood pressure goals may vary based upon the patient’s risk.

2 DOSAGE AND ADMINISTRATION

2.1 General Considerations

Dose orally once daily. Dosage must be individualized and may be increased after 2 weeks of treatment. Almost all the antihypertensive effect is apparent within 2 weeks of initiating treatment. Swallow tablets whole. Do not cut, crush, or chew tablets. Widaplik may be taken with or without food.

Correct imbalances of intravascular volume- or salt-depletion, before initiating therapy with Widaplik [see Warnings and Precautions (5.3)].

2.2 Recommended Dosage

The recommended starting dosage is with Widaplik (10 mg/1.25 mg/0.625 mg) orally once daily or Widaplik (20 mg/2.5 mg/1.25 mg) orally once daily, based on anticipated need for blood pressure reduction.

In elderly patients consider starting with Widaplik (10 mg/1.25 mg/0.625 mg) orally once daily [see Use in Specific Populations, Geriatric Use (8.5)].

The maximum recommended dose is Widaplik (40 mg/5 mg/2.5 mg) orally once daily.

3 DOSAGE FORMS AND STRENGTHS

Widaplik tablets are available as follows:

- 10 mg/1.25 mg/0.625 mg: 10 mg telmisartan/1.25 mg amlodipine/0.625 mg indapamide tablets – white to off-white oval tablet, debossed with “ULD” on one side and plain on the other side.
- 20 mg/2.5 mg/1.25 mg: 20 mg telmisartan/2.5 mg amlodipine/1.25 mg indapamide tablets – white to off-white round tablet, debossed with “LD” on one side and plain on the other side.
- 40 mg/5 mg/2.5 mg: 40 mg telmisartan/5 mg amlodipine/2.5 mg indapamide tablets – white to off-white oval tablet, debossed with “SD” on one side and plain on the other side.

4 CONTRAINDICATIONS

Do not use in patients with anuria, known hypersensitivity (e.g., anaphylaxis or angioedema) to telmisartan, amlodipine, indapamide, or to other sulfonamide-derived drugs, or to any other component of this product.

Do not co-administer aliskiren with Widaplik in patients with diabetes [see Drug Interactions (7.1)].

5 WARNINGS AND PRECAUTIONS

5.1 Fetal Toxicity

Use of drugs that act on the renin-angiotensin-aldosterone system during the second and third trimesters of pregnancy reduces fetal renal function and increases fetal and neonatal morbidity and death. Resulting oligohydramnios can be associated with fetal lung hypoplasia and skeletal deformations. Potential neonatal adverse effects include skull hypoplasia, anuria, hypotension, renal failure, and death. When pregnancy is detected, discontinue Widaplik as soon as possible [see Use in Specific Populations (8.1)].

5.2 Hypotension

Widaplik can cause symptomatic hypotension. Patients with hypovolemia, salt depletion, or aortic stenosis are at increased risk. Monitor blood pressure and adjust dose as needed.

Hypotension leading to worsening angina and acute myocardial infarction can develop after starting or increasing the dose of Widaplik because of the amlodipine component, particularly in patients with severe obstructive coronary artery disease.

5.3 Electrolyte and Glucose Imbalances

Thiazide-like diuretics can cause hyponatremia, hypomagnesemia and hypokalemia and can also alter serum glucose and affect insulin requirements. Drugs that inhibit the renin angiotensin-aldosterone system can cause hyperkalemia. Patients with renal impairment or heart failure are at increased risk for hyperkalemia. Monitor serum electrolytes and glucose periodically.

5.4 Impaired Renal Function

Inhibiting the renin-angiotensin-aldosterone system or diuresis can precipitate renal dysfunction, oliguria and acute renal failure. Patients with severe congestive heart failure or renal dysfunction are at increased risk [see Clinical Pharmacology (12.3)]. Monitor renal function periodically and adjust dose as needed.

5.5 Acute Angle-Closure Glaucoma, Acute Myopia, and Choroidal Effusion

Sulfonamide or sulfonamide-derivative drugs, like indapamide, can cause an idiosyncratic reaction resulting in acute angle-closure glaucoma and elevated intraocular pressure with or without a noticeable acute myopic shift and/or choroidal effusions. Symptoms may include acute onset of decreased visual acuity or ocular pain and typically occur within hours to weeks of drug initiation. Untreated, the angle-closure glaucoma may result in permanent visual field loss. The primary treatment is to discontinue Widaplik as rapidly as possible. Prompt medical or surgical treatments may need to be considered if the intraocular pressure remains uncontrolled. Risk factors for developing acute angle-closure glaucoma may include a history of sulfonamide or penicillin allergy.

5.6 Hyperuricemia

Hyperuricemia may occur or frank gout may be precipitated in certain patients receiving thiazide-like diuretics.

6 ADVERSE REACTIONS

The following is discussed in more detail in other sections of the labeling:
• Fetal toxicity [see Warnings and Precautions (5.1)]
• Hypotension [see Warnings and Precautions (5.2)]
• Electrolyte and Glucose Imbalances [see Warnings and Precautions (5.3)]
• Impaired Renal Function [see Warnings and Precautions (5.4)]
• Acute Angle-Closure Glaucoma, Acute Myopia, and Choroidal Effusion [see Warnings and Precautions (5.5)]
• Hyperuricemia [see Warnings and Precautions (5.6)]

6.1 Clinical Trials Experience

Because clinical studies are conducted under widely varying conditions, adverse reactions rates observed in the clinical studies of a drug cannot be directly compared to rates in the clinical studies of another drug and may not reflect the rates observed in clinical practice.

Widaplik

Safety data were obtained from two randomized controlled studies that included 1,680 randomized patients with hypertension of whom 782 received Widaplik. Given the well-established safety profiles of the component medicines, only serious adverse events and the following adverse events of special interest were recorded: symptomatic hypotension, abnormal laboratory findings (sodium, potassium, uric acid, glucose, lipids, creatinine, eGFR), headache, peripheral edema, or other reason for discontinuation of study medication.

Study 1

In Study 1 (NCT04518306), 295 adult patients who were not receiving antihypertensive treatment for two weeks with baseline home systolic blood pressure 130-154 mmHg were randomized in a 2:2:1 ratio to Widaplik (10 mg/1.25 mg/0.625 mg), Widaplik (20 mg/2.5 mg/1.25 mg), or placebo. The study was 4 weeks in duration and randomized 232 patients to Widaplik and 63 to placebo.

The proportion of patients who discontinued study medication due to an adverse event was 0% for Widaplik (10 mg/1.25 mg/0.625 mg), 5.1% for Widaplik (20 mg/2.5 mg/1.25 mg), and 1.6% for placebo. Symptomatic hypotension, hyponatremia, and hypokalemia were more common with Widaplik than placebo (see Table 1). Most cases were mild to moderate in severity.

Table 1: Adverse Reactions Reported in >2% of Patients Treated with Widaplik during the 4-Week Placebo-Controlled Treatment Period of Study 1

 | Widaplik (10 mg/1.25 mg/0.625 mg) (n=113) | Widaplik (20 mg/2.5 mg/1.25 mg) (n=118) | Placebo (n=62)
Symptomatic hypotension n (%) | 4 (3.5%) | 6 (5.1%) | 0 (0%)
Sodium <135 mmol/L at week 4, n (%) | 4 (3.5%) | 1 (0.8%) | 0 (0%)
Potassium <3.5 mmol/L at week 4, n (%) | 4 (3.5%) | 6 (5.1%) | 1 (1.6%)

Study 2

Study 2 (NCT04518293) enrolled 2,242 patients on 0-3 antihypertensive medications at the screening visit. After a 4-week active run-in period during which all patients were initially switched to Widaplik (20 mg/2.5 mg/1.25 mg), patients then entered a double-blind period where they were randomized 2:1:1:1 to either continue on Widaplik (20 mg/2.5 mg/1.25 mg) or switch to telmisartan/amlodipine (TA) 20 mg/2.5 mg, telmisartan/indapamide (TI) 20 mg/1.25 mg, or amlodipine/indapamide (AI) 2.5 mg/1.25 mg. After 6 weeks in the double-blind period, doses were doubled in all treatment groups and treatment was continued for an additional 6 weeks. The study randomized 551 patients to Widaplik and 834 to one of the two-drug combinations.

During the 4-week active run-in period on Widaplik, 3.2% of patients had symptomatic hypotension. During the run-in period, 3.2% of patients discontinued study medication due to an adverse event, including 0.8% of patients who discontinued due to symptomatic hypotension. Because of this run-in design, the proportion of patients with adverse reactions described below is lower than expected in practice (see Table 2). The proportion of patients who discontinued study medication due to an adverse event over the 12-week treatment period was 2.0% for Widaplik and 1.4%, 1.1%, and 1.4% for the telmisartan/indapamide, telmisartan/amlodipine, and amlodipine/indapamide groups, respectively. Most adverse reactions were generally mild to moderate in severity.

Table 2: Adverse Reactions Reported in >2% of Patients Treated with Widaplik during the 12-Week Treatment Period of Study 2

 | Widaplik (n = 547) | Telmisartan/ Indapamide (n = 275) | Telmisartan/ Amlodipine (n = 282) | Amlodipine/ Indapamide (n = 276)
Symptomatic hypotension, n (%) | 32 (5.9%) | 11 (4.0%) | 5 (1.8%) | 4 (1.4%)
Sodium <135 mmol/L at week 12, n (%) | 40 (7.3%) | 19 (6.9%) | 9 (3.2%) | 10 (3.6%)
Potassium <3.5 mmol/L at week 12, n (%) | 37 (6.8%) | 13 (4.7%) | 0 (0%) | 35 (12.7%)

6.2 Postmarketing Experience

The following additional adverse reactions have been reported in postmarketing experience with telmisartan, amlodipine or indapamide. Because these reactions are reported voluntarily from a population of uncertain size, it is not always possible to reliably estimate their frequency or establish a causal relationship to drug exposure.
Telmisartan
The most frequently reported events include: headache, dizziness, asthenia, coughing, nausea, fatigue, weakness, edema, face edema, lower limb edema, angioedema, urticaria, sweating increased, erythema, dyspepsia, diarrhea, pain, erectile dysfunction, abdominal pain, myalgia, eosinophilia, thrombocytopenia, anemia, and increased CPK, rhabdomyolysis, drug eruption (e.g., toxic skin eruption mostly reported as toxicoderma, rash, and urticaria).
Amlodipine
Jaundice and hepatic enzyme elevations (mostly consistent with cholestasis or hepatitis), extrapyramidal disorder.
Indapamide
Exacerbation of systemic lupus erythematous, choroidal effusion, acute myopia, and angle-closure glaucoma.

7 DRUG INTERACTIONS

7.1 Drug Interactions with Telmisartan

Aliskiren and other renin-angiotensin-aldosterone system (RAAS) inhibitors: Do not co-administer aliskiren with Widaplik in patients with diabetes. Most patients receiving the combination of two RAAS inhibitors do not obtain any additional benefit compared to monotherapy [see Contraindications (4)]. Avoid use of aliskiren with Widaplik in patients with renal impairment (GFR <60 mL/min) [see Warnings and Precautions (5.4)].

Digoxin: When telmisartan was co-administered with digoxin, median increases in digoxin peak plasma concentration (49%) and in trough concentration (20%) were observed. Monitor digoxin levels when initiating, adjusting, and discontinuing Widaplik to keep the digoxin level within the therapeutic range.

Lithium: Increases in serum lithium concentrations and toxicity have been reported during concomitant administration of lithium with angiotensin II receptor antagonists including telmisartan. Monitor serum lithium levels during concomitant use [see Drug Interactions with Indapamide (7.3)].

Non-Steroidal Anti-Inflammatory Agents including Selective Cyclooxygenase-2 Inhibitors (COX-2 Inhibitors): In patients who are elderly, volume-depleted (including those on diuretic therapy), or with compromised renal function, co-administration of NSAIDs, including selective COX-2 inhibitors, with angiotensin II receptor antagonists, including telmisartan, may result in deterioration of renal function, including possible acute renal failure. These effects are usually reversible. Monitor renal function periodically in patients receiving Widaplik and NSAID therapy.

The antihypertensive effect of angiotensin II receptor antagonists, including telmisartan may be attenuated by NSAIDs including selective COX-2 inhibitors.

7.2 Drug Interactions with Amlodipine

Impact of other drugs on amlodipine

CYP3A Inhibitors

Co-administration with CYP3A inhibitors (moderate and strong) results in increased systemic exposure to amlodipine and may require dose reduction. Monitor for symptoms of hypotension and edema when Widaplik is co-administered with CYP3A inhibitors to determine the need for dose adjustment.

CYP3A Inducers

No information is available on the quantitative effects of CYP3A inducers on amlodipine.

Blood pressure should be closely monitored when Widaplik is co-administered with CYP3A inducers.

Sildenafil

Monitor for hypotension when sildenafil is co-administered with Widaplik.

Impact of amlodipine on other drugs

Simvastatin: Co-administration of simvastatin with amlodipine increases the systemic exposure of simvastatin. Limit the dose of simvastatin in patients on Widaplik to 20 mg daily.

Immunosuppressants: Amlodipine may increase the systemic exposure of cyclosporine or tacrolimus when co-administered. Frequent monitoring of trough blood levels of cyclosporine and tacrolimus and dose adjustment when appropriate is recommended.

7.3 Drug Interactions with Indapamide

Lithium: In general, diuretics should not be given concomitantly with lithium because they reduce its renal clearance and add a high risk of lithium toxicity. Read prescribing information for lithium preparations before use of such concomitant therapy.

Norepinephrine: Indapamide, like thiazide diuretics, may decrease arterial responsiveness to norepinephrine, but this diminution is not sufficient to preclude effectiveness of the pressor agent for therapeutic use.

8 USE IN SPECIFIC POPULATIONS

8.1 Pregnancy

Risk Summary

Widaplik can cause fetal harm when administered to a pregnant woman. Use of drugs that act on the renin-angiotensin-aldosterone system during the second and third trimesters of pregnancy reduces fetal renal function and increases fetal and neonatal morbidity and death (see Clinical Considerations). Most epidemiologic studies examining fetal abnormalities after exposure to antihypertensive use in the first trimester have not distinguished drugs affecting the renin-angiotensin-aldosterone system from other antihypertensive agents. Studies in rats and rabbits showed fetotoxicity only at maternally toxic doses of telmisartan (see Data). When pregnancy is detected, discontinue Widaplik as soon as possible.

The estimated background risk of major birth defects and miscarriage for the indicated population is unknown. All pregnancies have a background risk of birth defect, loss, or other adverse outcomes. In the U.S. general population, the estimated background risk of major malformations and miscarriage in clinically recognized pregnancies is 2% to 4%, and 15% to 20%, respectively.

Clinical Considerations

Disease-Associated Maternal and/or Embryo/Fetal Risk

Hypertension in pregnancy increases the maternal risk for pre-eclampsia, gestational diabetes, premature delivery, and delivery complications (e.g., need for cesarean section, and post-partum hemorrhage). Hypertension increases the fetal risk for intrauterine growth restriction and intrauterine death. Pregnant women with hypertension should be carefully monitored and managed accordingly.

Fetal/Neonatal Adverse Reactions

Telmisartan

Use of drugs that act on the RAAS in the second and third trimesters of pregnancy can result in the following: oligohydramnios, reduced fetal renal function leading to anuria and renal failure, fetal lung hypoplasia, skeletal deformations, including skull hypoplasia, hypotension, and death. In the unusual case that there is no appropriate alternative to therapy with drugs affecting the renin-angiotensin-aldosterone system for a particular patient, apprise the mother of the potential risk to the fetus.

In patients taking Widaplik during pregnancy, perform serial ultrasound examinations to assess the intra-amniotic environment. Fetal testing may be appropriate, based on the week of gestation. If oligohydramnios is observed, discontinue Widaplik, unless it is considered lifesaving for the mother. Patients and physicians should be aware, however, that oligohydramnios may not appear until after the fetus has sustained irreversible injury. Closely observe neonates with histories of in utero exposure to Widaplik for hypotension, oliguria, and hyperkalemia. If oliguria or hypotension occurs, support blood pressure and renal perfusion. Exchange transfusions or dialysis may be required as a means of reversing hypotension and/or substituting for disordered renal function.

Indapamide

Diuretics are known to cross the placental barrier and appear in cord blood. There may be hazards associated with this use such as fetal or neonatal jaundice, thrombocytopenia, and possibly other adverse reactions that have occurred in the adult.

Data

Animal Data

No reproductive toxicity studies have been conducted with Widaplik. However, these studies have been conducted for telmisartan, amlodipine and indapamide alone.

Telmisartan

No teratogenic effects were observed when telmisartan was administered to pregnant rats at oral doses of up to 50 mg/kg/day and to pregnant rabbits at oral doses up to 45 mg/kg/day. In rabbits, embryolethality associated with maternal toxicity (reduced body weight gain and food consumption) was observed at 45 mg/kg/day [about 12 times the maximum recommended human dose (MRHD) of 80 mg on a mg/m^2 basis]. In rats, maternally toxic (reduction in body weight gain and food consumption) telmisartan doses of 15 mg/kg/day (about 1.9 times the MRHD on a mg/m^2 basis), administered during late gestation and lactation, were observed to produce adverse effects in neonates, including reduced viability, low birth weight, delayed maturation, and decreased weight gain. The no observed effect doses for developmental toxicity in rats and rabbits, 5 and 15 mg/kg/day, respectively, are about 0.64 and 3.7 times, on a mg/m^2 basis, the MHRD of telmisartan (80 mg/day).

Amlodipine

No evidence of teratogenicity or embryo/fetal toxicity was found when pregnant rats and rabbits were treated orally with amlodipine maleate at doses up to 10 mg amlodipine/kg/day (approximately 10 and 20 times the MRHD based on body surface area, respectively) during their respective periods of major organogenesis. However, for rats, litter size was significantly decreased (by about 50%) and the number of intrauterine deaths was significantly increased (about 5-fold). Amlodipine has been shown to prolong both the gestation period and the duration of labor in rats at this dose.

Indapamide

Reproduction studies have been performed in rats, mice and rabbits at doses up to 6,250 times the therapeutic human dose and have revealed no evidence of impaired fertility or harm to the fetus due to indapamide. Postnatal development in rats and mice was unaffected by pretreatment of parent animals during gestation.

8.2 Lactation

Risk Summary

There is no information regarding the presence of Widaplik in human milk, the effects on the breastfed infant, or the effects on milk production. Limited published studies report that amlodipine is present in human milk at an estimated median relative infant dose of 4.2%. No adverse effects of amlodipine on the breastfed infant have been observed. There is no available information on the effects of amlodipine on milk production. There is no information regarding the presence of telmisartan in human milk. Telmisartan is present in the milk of lactating rats (see Data). It is not known whether indapamide is excreted in human milk. Because of the potential for serious adverse reactions in the breastfed infant including hypotension, hyperkalemia and renal impairment, advise a nursing woman not to breastfeed during treatment with Widaplik.

Data

Telmisartan was present in the milk of lactating rats at concentrations 1.5 to 2 times those found in plasma from 4 to 8 hours after administration.

8.4 Pediatric Use

Safety and effectiveness of Widaplik in pediatric patients have not been established.

Neonates with a history of in utero exposure to Widaplik

If oliguria or hypotension occurs, support blood pressure and renal perfusion. Exchange transfusions or dialysis may be required as a means of reversing hypotension and/or substituting for disordered renal function.

8.5 Geriatric Use

Widaplik

In subgroup analysis in subjects ≥65 years (n= 176) the antihypertensive effect of Widaplik was not substantially different compared to younger subjects, however the number of elderly patients enrolled in both Widaplik studies was small.

Telmisartan

Of the total number of patients receiving telmisartan in clinical studies, 551 (18.6%) were 65 to 74 years of age and 130 (4.4%) were 75 years and older. No overall differences in effectiveness and safety were observed in these patients compared to younger patients and other reported clinical experience has not identified differences in responses between the elderly and younger patients, but greater sensitivity of some older individuals cannot be ruled out.

Amlodipine

Clinical studies with amlodipine did not include sufficient numbers of subjects aged 65 and over to determine whether they respond differently from younger subjects. Other reported clinical experience has not identified differences in responses between the elderly and younger patients. In general, dose selection for an elderly patient should be cautious, usually starting at the low end of the dosing range, reflecting the greater frequency of decreased hepatic, renal or cardiac function, and of concomitant disease or other drug therapy.

Since elderly patients may have decreased clearance of amlodipine, start amlodipine at ≤2.5 mg [see Dosage and Administration (2)].

Indapamide

Clinical studies with indapamide did not include sufficient numbers of subjects aged 65 and over to determine whether they respond differently from younger subjects. Other reported clinical experience has not identified differences in responses between the elderly and younger patients. In general, dose selection for an elderly patient should be cautious, usually starting at the low end of the dosing range, reflecting the greater frequency of decreased hepatic, renal or cardiac function, and of concomitant disease or other drug therapy.

Severe cases of hyponatremia, accompanied by hypokalemia have been reported with indapamide in elderly females [see Warnings and Precautions (5.3)].

8.6 Hepatic Impairment

Because telmisartan, amlodipine and indapamide are hepatically cleared, initiate therapy at the lowest dose and titrate slowly [see Clinical Pharmacology (12.3)]. The use of thiazide-like diuretics may precipitate hepatic coma because of fluid shifts.

10 OVERDOSAGE

Telmisartan

Limited data are available with regard to overdosage in humans. The most likely manifestations of overdosage would be hypotension, dizziness, and tachycardia; bradycardia could occur from parasympathetic (vagal) stimulation. If symptomatic hypotension should occur, supportive treatment should be instituted. Telmisartan is not removed by hemodialysis.

Amlodipine

Overdosage might be expected to cause excessive peripheral vasodilation with marked hypotension and possibly a reflex tachycardia. In humans, experience with intentional overdosage of amlodipine is limited. Marked and potentially prolonged systemic hypotension up to and including shock with fatal outcome have been reported.

Single oral doses of amlodipine maleate equivalent to 40 mg amlodipine/kg and 100 mg amlodipine/kg in mice and rats, respectively, caused deaths. Single oral amlodipine maleate doses equivalent to 4 or more mg amlodipine/kg or higher in dogs (11 or more times the MRHD on a mg/m^2 basis) caused a marked peripheral vasodilation and hypotension.

If massive overdose should occur, initiate active cardiac and respiratory monitoring. Frequent blood pressure measurements are essential. Should hypotension occur, provide cardiovascular support including elevation of the extremities and the judicious administration of fluids. If hypotension remains unresponsive to these conservative measures, consider administration of vasopressors (such as phenylephrine) with attention to circulating volume and urine output. As amlodipine is highly protein bound, hemodialysis is not likely to be of benefit. Administration of activated charcoal to healthy volunteers immediately or up to two hours after ingestion of amlodipine has been shown to significantly decrease amlodipine absorption.

Indapamide

Symptoms of overdosage of indapamide include nausea, vomiting, weakness, gastrointestinal disorders and disturbances of electrolyte balance. In severe instances, hypotension and depressed respiration may be observed. If this occurs, support of respiration and cardiac circulation should be instituted. There is no specific antidote. An evacuation of the stomach is recommended by emesis and gastric lavage after which the electrolyte and fluid balance should be evaluated carefully.

11 DESCRIPTION

Widaplik is a fixed dose combination of telmisartan, amlodipine and indapamide.

Widaplik contains telmisartan, a non-peptide angiotensin II receptor (type AT1) antagonist. Telmisartan is chemically described as 4'-[(1,4'-dimethyl-2'-propyl [2,6'-bi-1H-benzimidazol]-1'-yl)methyl]-[1,1'-biphenyl]-2-carboxylic acid. Its empirical formula is C33H30N4O2, its molecular weight is 514.63, and the structural formula is:

Telmisartan is a white to slightly yellowish solid. It is practically insoluble in water, slightly soluble in methanol and soluble in strong base.

Widaplik contains the besylate salt of amlodipine, a dihydropyridine calcium-channel blocker. Amlodipine besylate is chemically described as 3-ethyl-5-methyl (±)-2-[(2-aminoethoxy)methyl]-4-(2-chlorophenyl)-1,4-dihydro-6-methyl-3,5-pyridinedicarboxylate, monobenzenesulfonate. Its empirical formula is C20H25ClN2O5•C6H6O3S, its molecular weight is 567.1, and the structural formula is:

Amlodipine besylate is a white crystalline powder. It is slightly soluble in water and sparingly soluble in ethanol.

Widaplik contains indapamide, a thiazide-like diuretic. Indapamide is chemically described as 4-chloro-N-(2-methyl-1-indolinyl)-3-sulfamoylbenzamide. Its empirical formula is C16H16ClN3O3S, its molecular weight is 365.84, and the structural formula is:

Indapamide is a white to off-white, crystalline powder. It is soluble in ethyl alcohol and practically insoluble in water.

Widaplik tablets are formulated in 3 strengths for oral administration

- 10 mg/1.25 mg/0.625 mg: combination of 10 mg telmisartan, with 1.25 mg amlodipine (equivalent to 1.73 mg amlodipine besylate), with 0.625 mg indapamide
- 20 mg/2.5 mg/1.25 mg: combination of 20 mg telmisartan, with 2.5 mg amlodipine (equivalent to 3.47 mg amlodipine besylate), with 1.25 mg indapamide
- 40 mg/5 mg/2.5 mg: combination of 40 mg telmisartan, with 5 mg amlodipine (equivalent to 6.94 mg amlodipine besylate), with 2.5 mg of indapamide

Widaplik also contains the following inactive ingredients: croscarmellose sodium, magnesium stearate, mannitol, meglumine, microcrystalline cellulose, polyvinyl pyrrolidone, pregelatinized starch, and sodium hydroxide.

Widaplik tablets are hygroscopic and require protection from moisture. Widaplik tablets require protection from light.

12 CLINICAL PHARMACOLOGY

12.1 Mechanism of Action

The active ingredients of Widaplik target 3 separate mechanisms involved in blood pressure regulation.

Telmisartan

Angiotensin II is formed from angiotensin I in a reaction catalyzed by angiotensin-converting enzyme (ACE, kininase II). Angiotensin II is the principal pressor agent of the renin-angiotensin-aldosterone system, with effects that include vasoconstriction, stimulation of synthesis and release of aldosterone, cardiac stimulation, and renal reabsorption of sodium. Telmisartan blocks the vasoconstrictor and aldosterone-secreting effects of angiotensin II by selectively blocking the binding of angiotensin II to the AT1 receptor in many tissues, such as vascular smooth muscle and the adrenal gland. Its action is therefore independent of the pathways for angiotensin II synthesis.

There is also an AT2 receptor found in many tissues, but AT2 is not known to be associated with cardiovascular homeostasis. Telmisartan has much greater affinity (>3,000 fold) for the AT1 receptor than for the AT2 receptor. The increased plasma levels of angiotensin following AT1 receptor blockade with telmisartan may stimulate the unblocked AT2 receptor.

Blockade of the renin-angiotensin-aldosterone system with ACE inhibitors, which inhibit the biosynthesis of angiotensin II from angiotensin I, is widely used in the treatment of hypertension. ACE inhibitors also inhibit the degradation of bradykinin, a reaction also catalyzed by ACE. Because telmisartan does not inhibit ACE (kininase II), it does not affect the response to bradykinin. Whether this difference has clinical relevance is not yet known. Telmisartan does not bind to or block other hormone receptors or ion channels known to be important in cardiovascular regulation.

Blockade of the angiotensin II receptor inhibits the negative regulatory feedback of angiotensin II on renin secretion, but the resulting increased plasma renin activity and angiotensin II circulating levels do not overcome the effect of telmisartan on blood pressure.

Amlodipine

Amlodipine is a dihydropyridine calcium channel blocker that inhibits the transmembrane influx of calcium ions into vascular smooth muscle and cardiac muscle. Experimental data suggest that amlodipine binds to both dihydropyridine and non-dihydropyridine binding sites. The contractile processes of cardiac muscle and vascular smooth muscle are dependent upon the movement of extracellular calcium ions into these cells through specific ion channels. Amlodipine inhibits calcium ion influx across cell membranes selectively, with a greater effect on vascular smooth muscle cells than on cardiac muscle cells. Negative inotropic effects can be detected in vitro but such effects have not been seen in intact animals at therapeutic doses. Serum calcium concentration is not affected by amlodipine. Within the physiologic pH range, amlodipine is an ionized compound (pKa=8.6), and its kinetic interaction with the calcium channel receptor is characterized by a gradual rate of association and dissociation with the receptor binding site, resulting in a gradual onset of effect.

Amlodipine is a peripheral arterial vasodilator that acts directly on vascular smooth muscle to cause a reduction in peripheral vascular resistance and reduction in blood pressure.

Indapamide

Indapamide is a thiazide-like diuretic. Although the mechanism of action is not clear, indapamide appears to act principally on the distal convoluted tubules of the nephron. The drug enhances the excretion of sodium, chloride, and water by inhibiting the transport of sodium ions across the renal tubule. The hypovolemic action of indapamide is believed to be responsible for the drug's beneficial cardiovascular effects. Decreased plasma and extracellular fluid volume, along with a decreased peripheral vascular resistance (secondary to loss of sodium, or to vascular autoregulatory feedback systems), act to lower blood pressure in hypertensive patients who are receiving indapamide. The drug may also produce calcium-channel blockade in smooth muscle cells, thereby causing arteriolar vasodilation.

12.2 Pharmacodynamics

Widaplik is a combination of three drugs with antihypertensive properties: a dihydropyridine calcium antagonist (calcium ion antagonist or slow-channel blocker), amlodipine besylate, an angiotensin II receptor blocker, telmisartan and a thiazide-like diuretic, indapamide. All three components lower the blood pressure by reducing peripheral resistance, but through complementary mechanisms, each working at a separate site and blocking different effector pathways.

Widaplik has not been studied in indications other than hypertension.

Telmisartan

An oral dose of 80 mg telmisartan, a dose higher than in Widaplik, inhibited the pressor response of angiotensin II by about 90% at peak plasma concentrations with approximately 40% inhibition persisting for 24 hours.

Plasma concentration of angiotensin II and plasma renin activity (PRA) increased in a dose-dependent manner after single administration of telmisartan to healthy subjects and repeated administration to hypertensive patients. The once-daily administration of up to 80 mg telmisartan to healthy subjects did not influence plasma aldosterone concentrations. In multiple dose studies with hypertensive patients, there were no clinically significant changes in electrolytes (serum potassium or sodium), or in metabolic function (including serum levels of cholesterol, triglycerides, HDL, LDL, glucose, or uric acid).

In 30 hypertensive patients with normal renal function treated for 8 weeks with telmisartan 80 mg or telmisartan 80 mg in combination with hydrochlorothiazide 12.5 mg, there were no clinically significant changes from baseline in renal blood flow, glomerular filtration rate, filtration fraction, renovascular resistance, or creatinine clearance.

Amlodipine

Following administration of therapeutic doses to patients with hypertension, amlodipine produces vasodilation resulting in a reduction of supine and standing blood pressures. These decreases in blood pressure are not accompanied by a significant change in heart rate or plasma catecholamine levels with chronic dosing.

With chronic once daily administration, antihypertensive effectiveness is maintained for at least 24 hours. Plasma concentrations correlate with effect in both young and elderly patients. The magnitude of reduction in blood pressure with amlodipine is also correlated with the height of pretreatment elevation; thus, individuals with moderate hypertension (diastolic pressure 105 to 114 mmHg) had about a 50% greater response than patients with mild hypertension (diastolic pressure 90 to 104 mmHg). Normotensive subjects experienced no clinically significant change in blood pressure (+1/-2 mmHg).

In hypertensive patients with normal renal function, therapeutic doses of amlodipine resulted in a decrease in renal vascular resistance and an increase in glomerular filtration rate and effective renal plasma flow without change in filtration fraction or proteinuria.

As with other calcium channel blockers, hemodynamic measurements of cardiac function at rest and during exercise (or pacing) in patients with normal ventricular function treated with amlodipine have generally demonstrated a small increase in cardiac index without significant influence on dP/dt or on left ventricular end diastolic pressure or volume. In hemodynamic studies, amlodipine has not been associated with a negative inotropic effect when administered in the therapeutic dose range to intact animals and man, even when co-administered with beta-blockers to man. Similar findings, however, have been observed in normal or well-compensated patients with heart failure with agents possessing significant negative inotropic effects.

Amlodipine does not change sinoatrial nodal function or atrioventricular conduction in intact animals or man. In clinical studies in which amlodipine was administered in combination with beta-blockers to patients with either hypertension or angina, no adverse effects of electrocardiographic parameters were observed.

Pharmacodynamic Drug interactions

Sildenafil

When amlodipine and sildenafil were used in combination, each agent independently exerted its own blood pressure lowering effect [see Drug Interactions (7.2)].

12.3 Pharmacokinetics

Absorption

Following single-dose oral administration of Widaplik (40 mg/5 mg/2.5 mg) to healthy subjects in the fasted state, the extent of absorption (AUC) and rate of absorption (Cmax) of telmisartan was 750 ng.h/mL and 64.7 ng/mL, the AUC and Cmax of amlodipine was 102,000 pg.h/mL and 2,850 pg/mL, and the AUC and Cmax of indapamide was 2,170 ng.h/mL and 144 ng/mL, respectively. The peak plasma concentrations of telmisartan, amlodipine and indapamide are achieved at approximately 1.8 hours, 7.5 hours, and 0.9 hours, respectively, under fasting conditions.

Effect of Food

A food-effect study involving administration of Widaplik (40 mg/5 mg/2.5 mg) to healthy subjects after a high-fat, high calorie breakfast indicated that the Cmax of telmisartan decreased 41%, while AUC remained unchanged, the Cmax and AUC of amlodipine and indapamide remained unchanged, when compared to administration under fasting conditions. The Tmax of telmisartan, amlodipine and indapamide was delayed by approximately 2 hours, 1 hour, and 1.5 hours, respectively, under fed conditions.

Distribution

Telmisartan

Telmisartan is highly bound to plasma proteins (>99.5%), mainly albumin and α1-acid glycoprotein. Plasma protein binding is constant over the concentration range achieved with recommended doses. The volume of distribution for telmisartan is approximately 500 L indicating additional tissue binding.

Amlodipine

The apparent volume of distribution of amlodipine is 21 L/kg. Approximately 93% of circulating amlodipine is bound to plasma proteins in hypertensive patients.

Indapamide

Indapamide is preferentially and reversibly taken up by the erythrocytes in the peripheral blood. The whole blood/plasma ratio is approximately 6:1 at the time of peak concentration and decreases to 3.5:1 at eight hours. From 71 to 79% of the indapamide in plasma is reversibly bound to plasma proteins.

Metabolism and Elimination

Telmisartan

Following either intravenous or oral administration of ^14C-labeled telmisartan, most of the administered dose (>97%) was eliminated unchanged in feces via biliary excretion; only minute amounts were found in the urine (0.91% and 0.49% of total radioactivity, respectively).

Telmisartan is metabolized by conjugation to form a pharmacologically inactive acylglucuronide; the glucuronide of the parent compound is the only metabolite that has been identified in human plasma and urine. After a single dose, the glucuronide represents approximately 11% of the measured radioactivity in plasma. The cytochrome P450 isoenzymes are not involved in the metabolism of telmisartan.

Total plasma clearance of telmisartan is >800 mL/min. Terminal half-life and total clearance appear to be independent of dose.

Amlodipine

Amlodipine is extensively (about 90%) converted to inactive metabolites via hepatic metabolism with 10% of the parent compound and 60% of the metabolites excreted in the urine.

Elimination of amlodipine from the plasma is biphasic with a terminal elimination half-life of about 30 to 50 hours. Steady state plasma levels of amlodipine are reached after 7 to 8 days of consecutive daily dosing.

Indapamide

Indapamide is an extensively metabolized drug, with only about 7% of the total dose administered, recovered in the urine as unchanged drug during the first 48 hours after administration. The urinary elimination of ^14C-labeled indapamide and metabolites is biphasic with a terminal half-life of excretion of total radioactivity of 26 hours.

A minimum of 70% of a single oral dose is eliminated by the kidneys and an additional 23% by the gastrointestinal tract, probably including the biliary route. The half-life of indapamide in whole blood is approximately 14 hours.

Specific Populations

Geriatric Patients

Telmisartan: The pharmacokinetics of telmisartan do not differ between the elderly and those younger than 65 years.

Amlodipine: Elderly patients have decreased clearance of amlodipine with a resulting increase in AUC of approximately 40% to 60%.

Indapamide: The pharmacokinetics of indapamide in geriatric patients is unknown.

Male and Female Patients

Telmisartan: Plasma concentrations of telmisartan are generally 2 to 3 times higher in females than in males. In clinical trials, however, no significant increases in blood pressure response or in the incidence of orthostatic hypotension were found in women. No dosage adjustment is necessary.

Patients with Renal Impairment

Telmisartan: Renal impairment does not increase the AUC of telmisartan. Telmisartan is not removed from blood by hemodialysis.

Amlodipine: The pharmacokinetics of amlodipine are not significantly influenced by renal impairment.

Indapamide: The effect of renal impairment on the pharmacokinetics of indapamide is unknown.

Patients with Hepatic Impairment

Telmisartan: In patients with hepatic insufficiency, plasma concentrations of telmisartan are increased, and absolute bioavailability approaches 100% [see Use in Specific Populations (8.6)].

Amlodipine: Patients with hepatic insufficiency have decreased clearance of amlodipine with a resulting increase in AUC of approximately 40% to 60%.

Indapamide: The effect of hepatic impairment on the pharmacokinetics of indapamide is unknown [see Use in Specific Populations (8.6)].

Drug Interaction Studies

Telmisartan

Ramipril and Ramiprilat: Co-administration of telmisartan 80 mg once daily and ramipril 10 mg once daily to healthy subjects increases steady-state Cmax and AUC of ramipril 2.3- and 2.1-fold, respectively, and Cmax and AUC of ramiprilat 2.4- and 1.5-fold, respectively. In contrast, Cmax and AUC of telmisartan decrease by 31% and 16%, respectively. When co-administering telmisartan and ramipril, the response may be greater because of the possibly additive pharmacodynamic effects of the combined drugs, and also because of the increased exposure to ramipril and ramiprilat in the presence of telmisartan.

Other Drugs: Co-administration of telmisartan did not result in a clinically significant interaction with acetaminophen, amlodipine, glyburide, simvastatin, hydrochlorothiazide, warfarin, or ibuprofen. Telmisartan is not metabolized by the cytochrome P450 system and had no effects in vitro on cytochrome P450 enzymes, except for some inhibition of CYP2C19. Telmisartan is not expected to interact with drugs that inhibit cytochrome P450 enzymes; it is also not expected to interact with drugs metabolized by cytochrome P450 enzymes, except for possible inhibition of the metabolism of drugs metabolized by CYP2C19.

Amlodipine

In vitro data indicate that amlodipine has no effect on the human plasma protein binding of digoxin, phenytoin, warfarin, and indomethacin.

Impact of other drugs on amlodipine

Co-administered cimetidine, magnesium- and aluminum hydroxide antacids, sildenafil, and grapefruit juice have no impact on the exposure to amlodipine.

CYP3A inhibitors: Co-administration of a 180 mg daily dose of diltiazem with 5 mg amlodipine in elderly hypertensive patients resulted in a 60% increase in amlodipine systemic exposure. Erythromycin co-administration in healthy volunteers did not significantly change amlodipine systemic exposure. However, strong inhibitors of CYP3A (e.g., itraconazole, clarithromycin) may increase the plasma concentrations of amlodipine to a greater extent [see Drug Interactions (7.2)].

Impact of amlodipine on other drugs

Amlodipine is a weak inhibitor of CYP3A and may increase exposure to CYP3A substrates.

Co-administered amlodipine does not affect the exposure to atorvastatin, digoxin, ethanol and the warfarin prothrombin response time.

Simvastatin: Co-administration of multiple doses of 10 mg of amlodipine with 80 mg simvastatin resulted in a 77% increase in exposure to simvastatin compared to simvastatin alone [see Drug Interactions (7.2)].

Cyclosporine: A prospective study in renal transplant patients (N=11) showed on an average of 40% increase in trough cyclosporine levels when concomitantly treated with amlodipine [see Drug Interactions (7.2)].

Tacrolimus: A prospective study in healthy Chinese volunteers (N=9) with CYP3A5 expressers showed a 2.5- to 4-fold increase in tacrolimus exposure when concomitantly administered with amlodipine compared to tacrolimus alone. This finding was not observed in CYP3A5 non-expressers (N= 6). However, a 3-fold increase in plasma exposure to tacrolimus in a renal transplant patient (CYP3A5 non-expresser) upon initiation of amlodipine for the treatment of post-transplant hypertension resulting in reduction of tacrolimus dose has been reported. Irrespective of the CYP3A5 genotype status, the possibility of an interaction cannot be excluded with these drugs [see Drug Interactions (7.2)].

13 NONCLINICAL TOXICOLOGY

13.1 Carcinogenesis, Mutagenesis, Impairment of Fertility

Widaplik

No carcinogenicity, mutagenicity, or fertility studies have been conducted with this combination. However, these studies have been conducted for amlodipine, telmisartan and indapamide alone. Based on preclinical safety and human pharmacokinetic studies, there is no indication of any toxicologically significant adverse interaction between these components.

Telmisartan

There was no evidence of carcinogenicity when telmisartan was administered in the diet to mice and rats for up to 2 years. The highest doses administered to mice (1,000 mg/kg/day) and rats (100 mg/kg/day) are, on a mg/m^2 basis, about 59 and 13 times, respectively, the MRHD of telmisartan. These same doses have been shown to provide average systemic exposures to telmisartan >100 times and >25 times, respectively, the systemic exposure in humans receiving the MRHD (80 mg/day).

Genotoxicity assays did not reveal any telmisartan-related effects at either the gene or chromosome level. These assays included bacterial mutagenicity tests with Salmonella and E. coli (Ames), a gene mutation test with Chinese hamster V79 cells, a cytogenetic test with human lymphocytes, and a mouse micronucleus test.

No drug-related effects on the reproductive performance of male and female rats were noted at 100 mg/kg/day (the highest dose administered), about 13 times, on a mg/m^2 basis, the MRHD of telmisartan. This dose in the rat resulted in an average systemic exposure (telmisartan AUC as determined on day 6 of pregnancy) at least 50 times the average systemic exposure in humans at the MRHD (80 mg/day).

Amlodipine

Rats and mice treated with amlodipine maleate in the diet for up to two years, at concentrations calculated to provide daily dosage levels of 0.5 mg, 1.25 mg, and 2.5 mg amlodipine/kg/day, showed no evidence of a carcinogenic effect of the drug. For the mouse, the highest dose was, on mg/m^2 basis, similar to the MRHD of 10 mg amlodipine/day. For the rat, the highest dose was, on a mg/m^2 basis, about 2.5 times the MRHD (calculations based on a 60 kg patient).

Mutagenicity studies conducted with amlodipine maleate revealed no drug-related effects at either the gene or chromosome level.

There was no effect on the fertility of rats treated orally with amlodipine maleate (males for 64 days and females for 14 days prior to mating) at doses of up to 10 mg amlodipine/kg/day (about 10 times the MRHD of 10 mg/day on a mg/m^2 basis).

Indapamide

Both mouse and rat lifetime carcinogenicity studies were conducted. There was no significant difference in the incidence of tumors between the indapamide-treated animals (up to 100 mg/kg/day) and the control groups.

Doses up to 6,250 times the therapeutic human dose have revealed no evidence of impaired fertility as tested in rats, mice and rabbits.

14 CLINICAL STUDIES

The efficacy of Widaplik in lowering blood pressure was evaluated in a randomized study designed to evaluate the efficacy and safety of two doses of Widaplik (10 mg/1.25 mg/0.625 mg and 20 mg/2.5 mg/1.25 mg) compared to placebo (Study 1, NCT04518306) and in a randomized study designed to evaluate the efficacy and safety of Widaplik (40 mg/5 mg/2.5 mg) as compared to each of its two-drug combinations at the same doses (Study 2, NCT04518293).

Study 1

Study 1 (NCT04518306) was a 4-week, multi-center, randomized, double-blind, placebo-controlled, parallel group study that randomized 295 adults with systolic hypertension who were taking 0-1 antihypertensive medications at screening and who were at a low risk for cardiovascular disease per local guidelines (e.g., pooled cohorts equation 10-year atherosclerotic cardiovascular disease risk <10% in the United States). The study excluded patients with a clinic seated blood pressure ≥160/100 mmHg at screening and an estimated glomerular filtration rate (eGFR) <60 mL/min/1.73 m^2 at randomization. Following a 2-week placebo run-in period during which any monotherapy was discontinued, eligible patients with a home systolic blood pressure between 130 and 154 mmHg were randomized 2:2:1 to receive Widaplik (10 mg/1.25 mg/0.625 mg), Widaplik (20 mg/2.5 mg/1.25 mg), or placebo. The primary endpoint was the change from randomization to Week 4 in home systolic blood pressure.

At baseline, mean age was 51 years (range 19 to 83 years), 44% of patients were male, 61% were White, 17% Black, and 21% Asian.

The change from randomization to Week 4 in home systolic and diastolic pressure in the Widaplik (10 mg/1.25 mg/0.625 mg), Widaplik (20 mg/2.5 mg/1.25 mg), and placebo arms, is shown in Table 3. Both doses of Widaplik showed statistically significant greater reductions in home systolic blood pressure compared to placebo (see Table 3). Most of the home systolic blood pressure lowering effect occurred within the first two weeks of treatment with Widaplik for both doses. The findings for clinic blood pressure were consistent with the results for home blood pressure.

Table 3: Changes from Randomization to Week 4 in Home Blood Pressure, Comparing Widaplik (10 mg/1.25 mg/0.625 mg) or Widaplik (20 mg/2.5 mg/1.25 mg) vs Placebo (Study 1)

 | Placebo (N=63) | Widaplik 10 mg/1.25 mg/0.625 mg (N=113) | Widaplik 20 mg/2.5 mg/1.25 mg (N=119)
Home systolic blood pressure, mmHg
Randomization, Mean (SD) | 138.7 (6.9) | 138.4 (6.7) | 138.8 (6.3)
Week 4, Mean (SD) | 136.4 (8.9) | 129.2 (9.5) | 128.0 (12.0)
LSM change from randomization, Mean (SE) | -2.2 (1.2) | -9.6 (1.0) | -10.4 (1.3)
Difference to placebo in LSM (95% CI) P-value | - | -7.3 (-10.2, -4.5) p <0.0001 | -8.2 (-11.3, -5.2) p <0.0001
Home diastolic blood pressure, mmHg
Randomization, Mean (SD) | 85.8 (8.6) | 85.2 (7.3) | 86.9 (7.2)
LSM change from randomization, Mean (SE) | -1.1 (0.8) | -5.1 (0.8) | -6.6 (0.6)
Difference to placebo in LSM (95% CI) | - | -4.0 (-6.0, -2.0) | -5.5 (-7.3, -3.7)

CI= confidence interval; LSM = least squares mean; SD = standard deviation; SE = standard error.

Study 2

Study 2 (NCT04518293) was a 12-week, multi-center, randomized, double-blind, parallel group study designed to evaluate the efficacy of Widaplik up to 40 mg/5 mg/2.5 mg as compared to each of its two-drug combinations at the same doses: telmisartan/indapamide (TI), telmisartan/amlodipine (TA), or amlodipine/indapamide (AI).

Enrolled patients were required to have a mean systolic blood pressure of 140 to 179 mmHg if on no antihypertensive medications, 130 to 170 mmHg if on one, 120 to 160 mmHg if on two, or 110 to 150 mmHg if on three. The study excluded patients with a history of cardiovascular disease, New York Heart Association (NYHA) class III or IV congestive heart failure, or an eGFR <60 mL/min/ 1.73 m^2 at screening. Following discontinuation of any antihypertensive medications, 2,244 patients entered a 4-week, single-blind, run-in period where all patients received Widaplik (20 mg/2.5 mg/ 1.25 mg). After the 4-week run-in period, 1,385 patients with systolic blood pressure 110 to 154 mmHg were randomized 2:1:1:1 to Widaplik (20 mg/2.5 mg/1.25 mg); TA 20 mg/2.5 mg; TI 20 mg/1.25 mg; or AI 2.5 mg/1.25 mg. After Week 6 and through Week 12, doses in all 4 groups were doubled (Widaplik 40 mg/5 mg/2.5 mg, TA 40 mg/5 mg, TI 40 mg/2.5 mg, and AI 5 mg/2.5 mg). The primary endpoint was the change in home seated mean systolic blood pressure from randomization to Week 12.

At baseline, mean age was 59 years (range 20 to 91 years), 49% of patients were male, 46% were White, 5% were Black and 49% Asian.

The change from randomization to Week 12 in home systolic and diastolic blood pressure in the Widaplik (40 mg/5 mg/2.5 mg) arm and in each of the dual combination arms is shown in Table 4. Widaplik (40 mg/5 mg/2.5 mg) showed statistically significant greater reductions in home systolic blood pressure compared to each of the dual combinations. The findings for clinic blood pressure were consistent with the results for home blood pressure.

Table 4: Changes from Randomization to Week 12 in Home Blood Pressure, Comparing Widaplik (40 mg/5 mg/2.5 mg) vs TA 40 mg/5 mg, TI 40 mg/2.5 mg, and AI 5 mg/2.5 mg (Study 2)

 | Widaplik 40 mg/5 mg/2.5 mg (N=551) | Telmisartan/ Indapamide 40 mg/2.5 mg (N=276) | Telmisartan/ Amlodipine 40 mg/5 mg (N=282) | Amlodipine/ Indapamide 5 mg/2.5 mg (N=276)
Home systolic blood pressure, mmHg
Randomization, Mean (SD) | 128.7 (9.9) | 128.9 (10.6) | 128.4 (9.9) | 129.2 (9.8)
Week 12, Mean (SD) | 124.0 (10.4) | 126.5 (11.6) | 129.4 (11.1) | 128.8 (10.8)
LSM change from randomization, Mean (SE) | -4.0 (0.5) | -1.5 (0.5) | 1.4 (0.6) | 0.5 (0.4)
Difference Widaplik vs dual comparator in LSM (95% CI) P-value | - | -2.5 (-3.7, -1.3) p <0.0001 | -5.4 (-6.8, -4.1) p<0.0001 | -4.4 (-5.8, -3.1) p<0.0001
Home diastolic blood pressure, mmHg
Randomization, Mean (SD) | 78.0 (9.0) | 77.4 (8.5) | 78.4 (9.3) | 78.4 (8.6)
LSM change from randomization, Mean (SE) | -2.9 (0.3) | -0.8 (0.4) | 0.5 (0.3) | 0.7 (0.5)
Difference Widaplik vs dual comparator in LSM (95% CI) | - | -2.1 (-3.0, -1.2) | -3.4 (-4.1, -2.6) | -3.6 (-4.6, -2.6)

T=telmisartan, A=amlodipine, I=indapamide.

CI= confidence interval; LSM= least squares mean; SD= standard deviation; SE= standard error.

Widaplik’s blood pressure lowering effect appeared consistent among subgroups defined by age, sex, and race.

There are no studies of Widaplik demonstrating reductions in cardiovascular risk in patients with hypertension; however, previous studies with amlodipine, indapamide and several angiotensin II receptor blockers, which are in the same pharmacological class as the telmisartan component, have demonstrated such benefits.

16 HOW SUPPLIED/STORAGE AND HANDLING

Widaplik 10 mg/1.25 mg/0.625 mg: White to off-white oval tablet, debossed with “ULD” on one side and plain on other side.

Widaplik 20 mg/2.5 mg/1.25 mg: White to off-white round tablet, debossed with “LD” on one side and plain on other side.

Widaplik 40 mg/5 mg/2.5 mg: White to off-white oval tablet, debossed with “SD” on one side and plain on other side.

Widaplik tablets are supplied in the following strengths and package configurations:

Tablet strength (telmisartan/amlodipine/indapamide) | Package Configuration | NDC#
10 mg/1.25 mg/0.625 mg | Bottles of 30 tablets | 24338-001-30
20 mg/2.5 mg/1.25 mg | Bottles of 30 tablets | 24338-002-30
40 mg/5 mg/2.5 mg | Bottles of 30 tablets | 24338-003-30

Storage

Store at 20°C to 25°C (68°F to 77°F); excursions permitted between 15°C and 30°C (59°F and 86°F) [see USP Controlled Room Temperature]. Protect from moisture and light. Store and dispense the product in the original container.

17 PATIENT COUNSELING INFORMATION

Advise the patient to read the FDA-approved patient labelling (see Patient Information).

Pregnancy

Advise female patients of childbearing age about the consequences of exposure to Widaplik during pregnancy. Discuss treatment options with women planning to become pregnant. Tell patients to report pregnancies to their physicians as soon as possible [see Warnings and Precautions (5.1) and Use in Specific Populations (8.1)].

Lactation

Advise nursing women not to breastfeed during treatment with Widaplik [see Use in Specific Populations (8.2)].

Symptomatic Hypotension

Advise patients that lightheadedness can occur, especially during the first days of therapy, and to report it to their healthcare provider. Inform patients that inadequate fluid intake, excessive perspiration, diarrhea, or vomiting can lead to an excessive fall in blood pressure, with the same consequences of lightheadedness and possible syncope. Advise patients to contact their healthcare provider if syncope occurs [see Warnings and Precautions (5.2)].

Hyperuricemia

Advise patients to inform their healthcare provider if they experience signs or symptoms associated with hyperuricemia [see Warnings and Precautions (5.6)].

Potassium Supplements

Advise patients not to use potassium supplements or salt substitutes that contain potassium without consulting the prescribing healthcare provider [see Warnings and Precautions (5.3)].

WidaplikTM is a trademark of George Medicines Pty Limited and distributed by Azurity Pharmaceuticals, Inc.

Manufactured by:
Piramal Pharma Limited
Plot No. 67-70, Sector II,
Pithampur, Dist. Dhar,
Madhya Pradesh 454775, India

©2025 Azurity Pharmaceuticals, Inc.

ALL RIGHTS RESERVED

The other brands listed are trademarks of their owners.

Rev.00 AUG2025

Patient Package Insert

Patient Information
WIDAPLIKTM (wid-UH-plick)
(telmisartan, amlodipine, and indapamide)
Tablets, for oral use

What is the most important information I should know about Widaplik?
Widaplik can cause harm or death to an unborn baby. Talk to your healthcare provider about other ways to lower your blood pressure if you plan to become pregnant. If you get pregnant during treatment with Widaplik, stop taking Widaplik and tell your healthcare provider right away.

What is Widaplik?
Widaplik is a prescription medicine that contains telmisartan, amlodipine and indapamide.
Widaplik is used to treat high blood pressure (hypertension) in adults. Widaplik may be used as the first medicine to lower your high blood pressure if your healthcare provider decides you are likely to need more than one medicine.
It is not known if Widaplik is safe and effective in children.

Do not take Widaplik if you:

- have no urine output (anuria).
- are allergic to telmisartan, amlodipine, indapamide, or to other sulfonamide type medicines, or to any of the ingredients in Widaplik. See the end of this leaflet for a complete list of ingredients in Widaplik.
- have diabetes and are taking aliskiren.

Before taking Widaplik, tell your healthcare provider about all of your medical conditions, including if you:

- have liver problems
- have kidney problems
- have heart problems
- have imbalance of salts (electrolytes) and fluids in your body
- have glaucoma
- have an allergy to the medicines sulfonamide or penicillin
- have gout
- are pregnant or plan to become pregnant. See “What is the most important information I should know about Widaplik?”
- are breastfeeding or plan to breastfeed. It is not known if Widaplik passes into your breast milk. Do not breastfeed during treatment with Widaplik. Talk with your healthcare provider about the best way to feed your baby if you take Widaplik.

Tell your healthcare provider about all the medicines you take, including prescription and over-the-counter medicines, vitamins and herbal supplements.
Widaplik may affect the way other medicines work, and other medicines may affect how Widaplik works.
Especially tell your healthcare provider if you take:

- aliskiren
- digoxin
- lithium
- non-steroidal anti-inflammatory drugs (NSAIDs)
- simvastatin
- cyclosporine or tacrolimus
- norepinephrine

Know the medicines you take. Keep a list of them and show it to your healthcare provider or pharmacist when you get a new medicine.

How should I take Widaplik?

- Take Widaplik exactly as your healthcare provider tells you to take it.
- Your healthcare provider will tell you how much Widaplik to take and when to take it. Your healthcare provider may change your dose if needed.
- Take Widaplik 1 time each day.
- Swallow Widaplik tablets whole. Do not cut, crush, or chew tablets.
- Take Widaplik with or without food.
- If you take too much Widaplik, call your healthcare provider or go to the nearest hospital emergency room right away.

What are possible side effects of Widaplik?
Widaplik may cause serious side effects, including:

- harm or death to your unborn baby. See “What is the most important information I should know about Widaplik?”

- low blood pressure (hypotension). Low blood pressure can happen with Widaplik, especially during the first few days of starting treatment and can cause you to feel lightheaded. If you feel lightheaded, faint, or dizzy call your healthcare provider right away. Low blood pressure is most likely to happen if you:
  - take water pills (diuretics)
  - are on a low-salt diet
  - do not drink enough liquids
  - sweat excessively
  - have heart problems
  - get sick with vomiting or diarrhea

- changes in levels of body salt (electrolyte) and sugar (glucose) in your blood. Widaplik can cause low levels of sodium and magnesium in your blood and affect your blood glucose and potassium levels. Your healthcare provider will check your electrolyte and glucose levels during treatment with Widaplik. Do not use potassium supplements or salt substitutes that contain potassium without talking to your healthcare provider.
- kidney problems. Widaplik can cause kidney problems that can lead to decreased urine output and short-term (acute) kidney failure. Kidney problems may get worse if you already have kidney disease. People with severe congestive heart failure have an increased risk of kidney problems. Your healthcare provider will check your kidney function during treatment with Widaplik. Tell your healthcare provider if you get:
  - swelling in your feet, ankles, or hands
  - unexplained weight gain

- eye problems. One of the medicines in Widaplik can cause eye problems that may lead to vision loss. Symptoms of eye problems can happen within hours to weeks of starting Widaplik. Tell your healthcare provider right away if you have:
  - decrease in vision
  - eye pain

- increased uric acid levels in your blood (hyperuricemia). People who have increased levels of uric acid in the blood may develop gout.

Rare, serious allergic reactions may happen. Tell your healthcare provider right away if you get any of these symptoms:

- swelling of face, tongue, throat
- difficulty breathing
- rash or raised patches on your skin (hives)

The most common side effects of Widaplik include:
• low blood pressure
• low sodium and potassium levels in your blood
These are not all the possible side effects of Widaplik. Tell your healthcare provider if you have any side effect that bothers you or that does not go away.
Call your doctor for medical advice about side effects. You may report side effects to FDA at 1-800-FDA-1088.

How should I store Widaplik?

- Store Widaplik tablets at room temperature between 68°F to 77°F (20°C to 25°C).
- Keep Widaplik tablets out of the light and away from moisture.
- Store Widaplik tablets in the original container.

Keep Widaplik and all medicines out of the reach of children.

General information about the safe and effective use of Widaplik.
Medicines are sometimes prescribed for purposes other than those listed in a Patient Information leaflet. Do not use Widaplik for a condition for which it was not prescribed. Do not give Widaplik to other people, even if they have the same symptoms that you have. It may harm them. You can ask your pharmacist or healthcare provider for information about Widaplik that is written for health professionals.

What are the ingredients in Widaplik?
Active ingredients: telmisartan, amlodipine besylate and indapamide.
Inactive ingredients: croscarmellose sodium, magnesium stearate, mannitol, meglumine, microcrystalline cellulose, polyvinyl pyrrolidone, pregelatinized starch, and sodium hydroxide.
Manufactured by: Piramal Pharma Limited, Plot No. 67-70, Sector II, Pithampur, Dist. Dhar, Madhya, Pradesh 454775, India
For more information, call Azurity Pharmaceuticals, Inc. at 1-800-461-7449 or visit www.widaplik.com.

This Patient Information has been approved by the U.S. Food and Drug Administration Revised: AUG/2025

PRINCIPAL DISPLAY PANEL - Widaplik ULD (10 mg/1.25 mg/0.625 mg) Bottle

NDC 24338-001-30

Widaplik™

(telmisartan, amlodipine and indapamide) tablets

10 mg/1.25 mg/0.625 mg

Swallow tablets whole.

Do not cut, crush or chew tablets.

Rx Only

30 Tablets

PRINCIPAL DISPLAY PANEL - Widaplik LD (20 mg/2.5 mg/1.25 mg) Bottle

NDC 24338-002-30

Widaplik™

(telmisartan, amlodipine and indapamide) tablets

20 mg/2.5 mg/1.25 mg

Swallow tablets whole.

Do not cut, crush or chew tablets.

RxOnly

30 Tablets

PRINCIPAL DISPLAY PANEL - Widaplik SD (40 mg/5 mg/2.5 mg) Bottle

NDC 24338-003-30

Widaplik™

(telmisartan, amlodipine and indapamide) tablets

40 mg/5 mg/2.5 mg

Swallow tablets whole.

Do not cut, crush or chew tablets.

RxOnly

30 Tablets